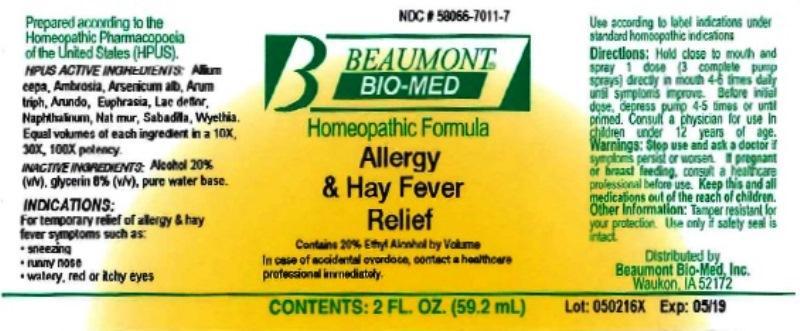 DRUG LABEL: Allergy and Hay Fever Relief
NDC: 58066-7011 | Form: LIQUID
Manufacturer: Beaumont Bio Med
Category: homeopathic | Type: HUMAN OTC DRUG LABEL
Date: 20160907

ACTIVE INGREDIENTS: ONION 10 [hp_X]/59.2 mL; AMBROSIA ARTEMISIIFOLIA 10 [hp_X]/59.2 mL; ARSENIC TRIOXIDE 10 [hp_X]/59.2 mL; ARISAEMA TRIPHYLLUM ROOT 10 [hp_X]/59.2 mL; ARUNDO PLINIANA ROOT 10 [hp_X]/59.2 mL; EUPHRASIA STRICTA 10 [hp_X]/59.2 mL; SKIM MILK 10 [hp_X]/59.2 mL; NAPHTHALENE 10 [hp_X]/59.2 mL; SODIUM CHLORIDE 10 [hp_X]/59.2 mL; SCHOENOCAULON OFFICINALE SEED 10 [hp_X]/59.2 mL; WYETHIA HELENIOIDES ROOT 10 [hp_X]/59.2 mL
INACTIVE INGREDIENTS: ALCOHOL; GLYCERIN; WATER

Allergy and Hay Fever Relief

ACTIVE INGREDIENT

HPUS Active Ingredients: Allium cepa, Ambrosia artemisiaefolia, Arsenicum album, Arum triphyllum, Arundo mauritanica, Euphrasia officinalis, Lac defloratum, Naphthalinum, Natrum muriaticum, Sabadilla, Wyethia helenioides. Equal volumes of each ingredient in 10X, 30X, 100X potencies.

INACTIVE INGREDIENT

Inactive Ingredients: Alcohol @ 20% (v/v), Glycerin @ 8% (v/v), in a pure water base.

INDICATIONS AND USAGE

Indications: For temporary relief of allergy and hay fever symptoms such as: sneezing, runny nose, watery, red or itchy eyes.

Use according to label indications and/or standard homeopathic indications.

Directions:

- Hold close to mouth and spray 1 dose (3 complete pump sprays) directly in mouth 4-6 times daily until symptoms improve.
- Before initial dose, depress pump 4-5 times or until primed.
- Consult a physician for use in children under 12 years of age.

WARNINGS

Warnings: If symptoms persist or get worse, consult a physician. If you are pregnant or nursing seek the advice of a physician before using this product. Keep this and all medications out of the reach of children. Do not use if bottle seal is broken or tampered with.

- Keep out of reach of children.

Other Information: Tamper resistant for your protection. Use only if safety seal is intact.

PURPOSE

For temporary relief of allergy and hay fever symptoms such as:

- sneezing
- runny nose
- watery, red or itchy eyes

Use according to label indications and/or standard homeopathic indications.